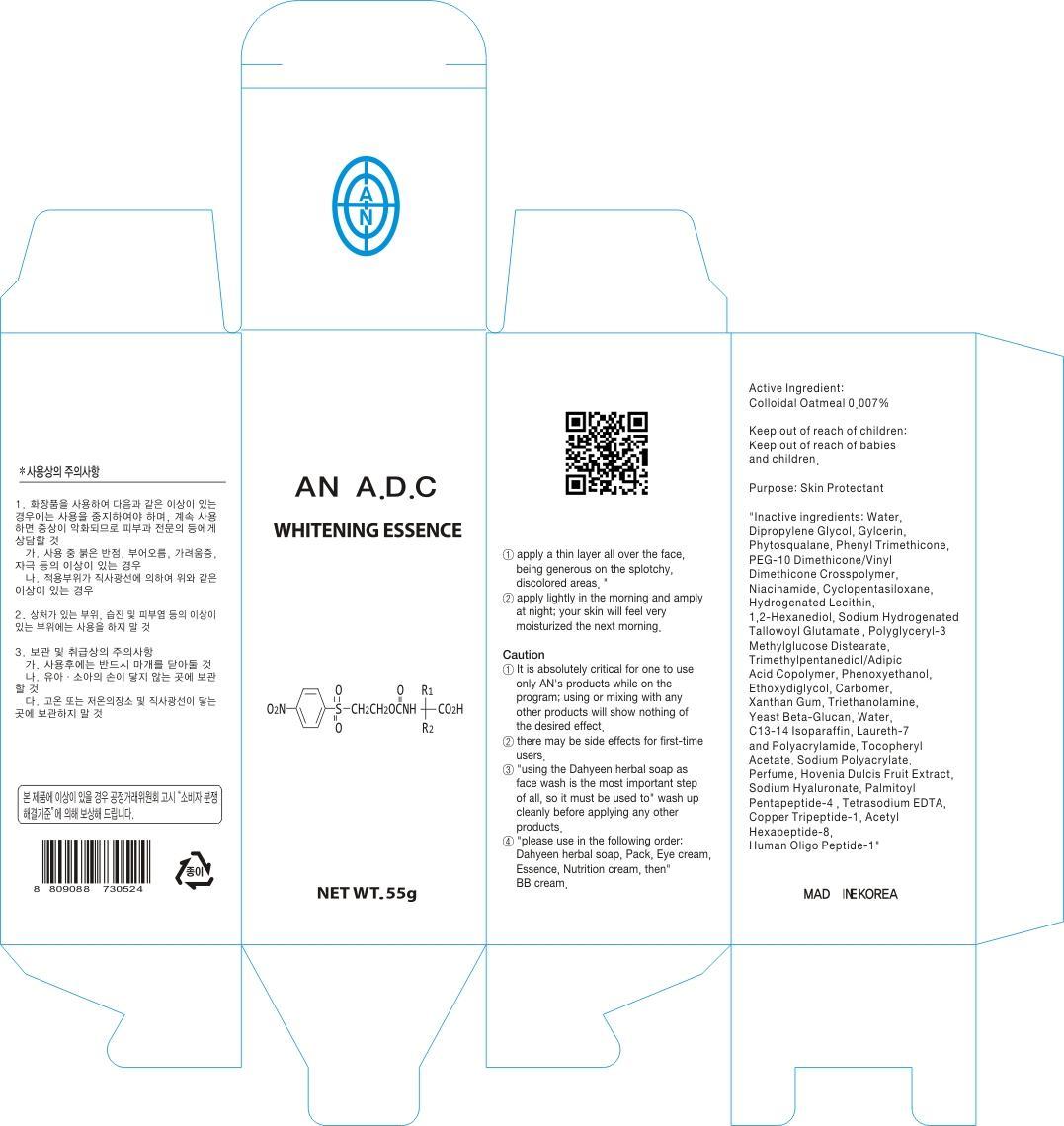 DRUG LABEL: AN ADC WHITENING ESSENCE
NDC: 69153-040 | Form: CREAM
Manufacturer: AN Co Ltd.
Category: otc | Type: HUMAN OTC DRUG LABEL
Date: 20140929

ACTIVE INGREDIENTS: OATMEAL 0.003 g/55 g
INACTIVE INGREDIENTS: Water; Dipropylene Glycol

ACTIVE INGREDIENT

Active Ingredient: Colloidal Oatmeal 0.007%

INACTIVE INGREDIENT

Inactive ingredients: Water, Dipropylene Glycol, Phytosqualane, Gylcerin, Phenyl Trimethicone, PEG-10 Dimethicone/Vinyl Dimethicone Crosspolymer, Niacinamide, Cyclopentasiloxane, Hydrogenated Lecithin, 1,2-Hexanediol, Sodium Hydrogenated Tallowoyl Glutamate , Polyglyceryl-3 Methylglucose Distearate, Trimethylpentanediol/Adipic Acid Copolymer, Phenoxyethanol, Ethoxydiglycol, Carbomer, Xanthan Gum, Triethanolamine, Yeast Beta-Glucan, Water, C13-14 Isoparaffin, Laureth-7 and Polyacrylamide, Tocopheryl Acetate, Sodium Polyacrylate, Perfume, Hovenia Dulcis Fruit Extract, Sodium Hyaluronate, Palmitoyl Pentapeptide-4 , Tetrasodium EDTA, Copper Tripeptide-1, Acetyl Hexapeptide-8, Human Oligo Peptide-1

PURPOSE

Purpose: Skin Protectant

Caution

1. It is absolutely critical for one to use only AN's products while on the program; using or mixing with any other products will show nothing of the desired effect.
2. There may be side effects for first-time users.
3. Using the Dahyeen herbal soap as face wash is the most important step of all, so it must be used to wash up cleanly before applying any other products.
4. Please use in the following order: Dahyeen herbal soap, Pack, Eye cream, Essence, Nutrition cream, then BB cream.

Keep out of reach of children: Keep out of reach of babies and children.

INDICATIONS & USAGE

1. Apply a thin layer all over the face, being generous on the splotchy, discolored areas.
2. Apply lightly in the morning and amply at night; your skin will feel very moisturized the next morning.

DOSAGE & ADMINISTRATION

1. Apply a thin layer all over the face, being generous on the splotchy, discolored areas.
2. Apply lightly in the morning and amply at night; your skin will feel very moisturized the next morning.